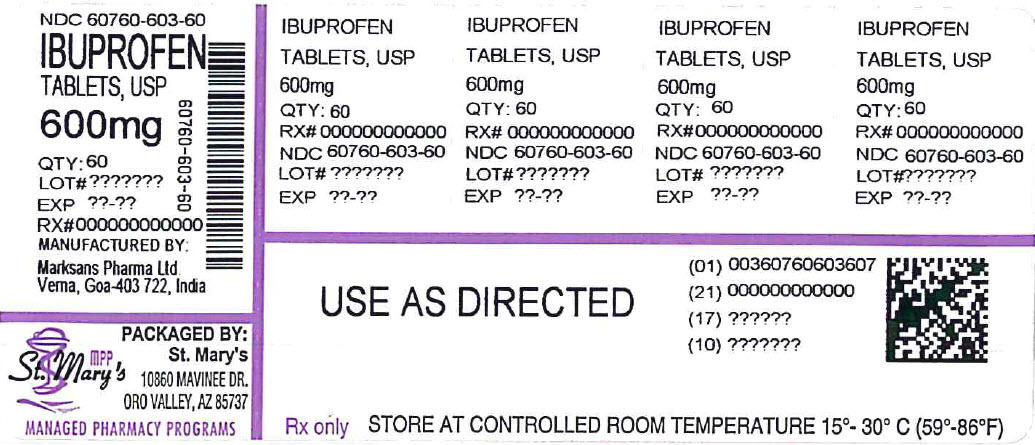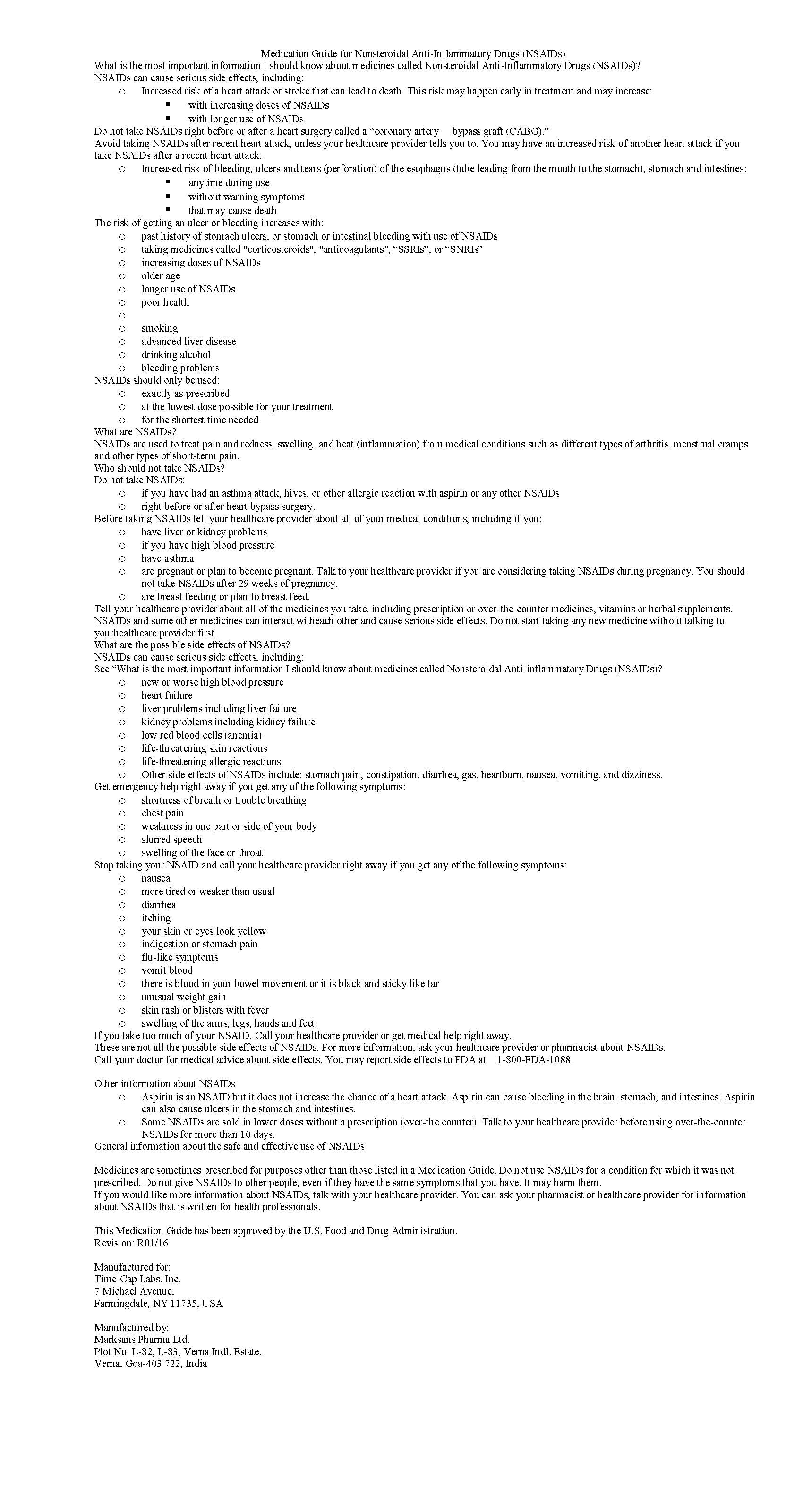 DRUG LABEL: IBUPROFEN
NDC: 60760-603 | Form: TABLET, FILM COATED
Manufacturer: St. Mary's Medical Park Pharmacy
Category: prescription | Type: HUMAN PRESCRIPTION DRUG LABEL
Date: 20230217

ACTIVE INGREDIENTS: IBUPROFEN 600 mg/1 1
INACTIVE INGREDIENTS: POLYVINYL ALCOHOL; STARCH, PREGELATINIZED CORN; TALC; TITANIUM DIOXIDE; SILICON DIOXIDE; CROSCARMELLOSE SODIUM; MAGNESIUM STEARATE; CELLULOSE, MICROCRYSTALLINE; POLYETHYLENE GLYCOL, UNSPECIFIED

IBUPROFEN 400 MG - 600 MG AND 800 MG TABLETS

HOW SUPPLIED

600mg (white to off white, capsule shaped, biconvex, film coated tablets debossed with '122' on one side and plain on the other side)

NDC

60760-603-20 BOTTLES OF 20

60760-603-28 BOTTLES OF 28

60760-603-30 BOTTLES OF 30

60760-603-40 BOTTLES OF 40

60760-603-60 BOTTLES OF 60

60760-603-90 BOTTLES OF 90